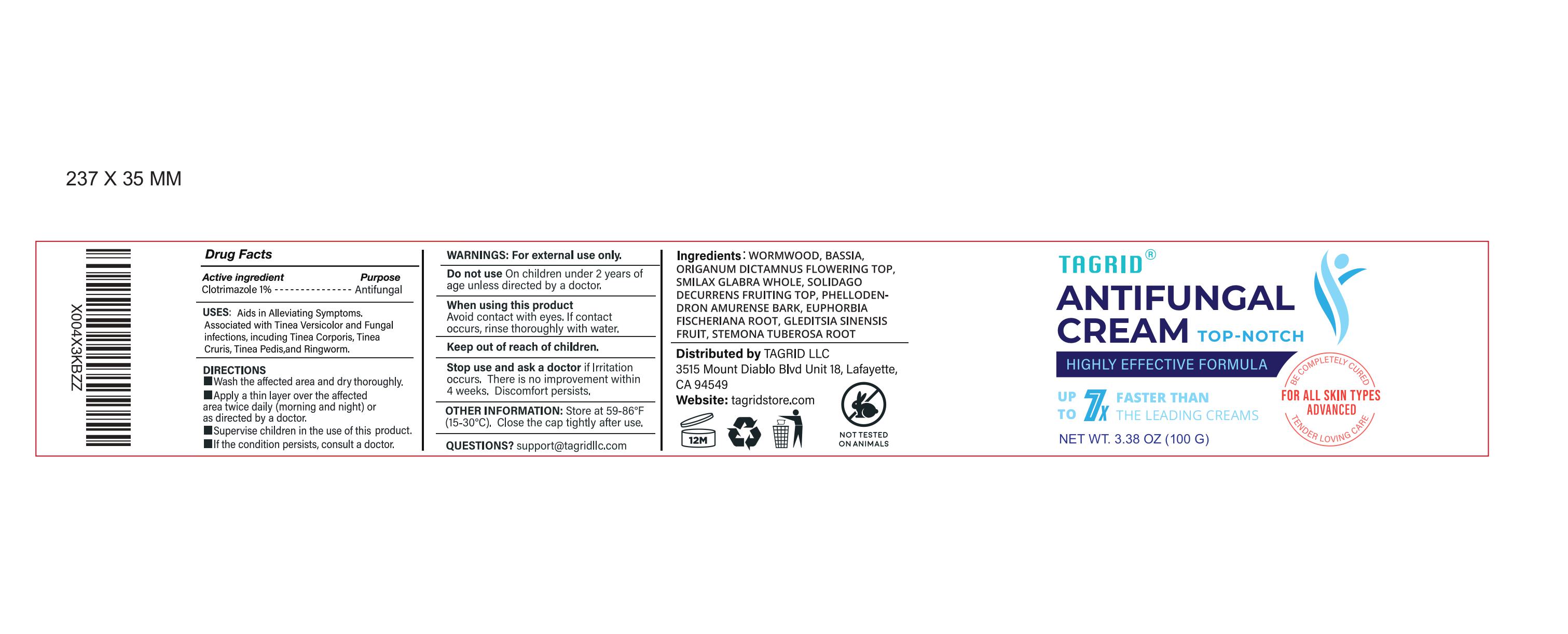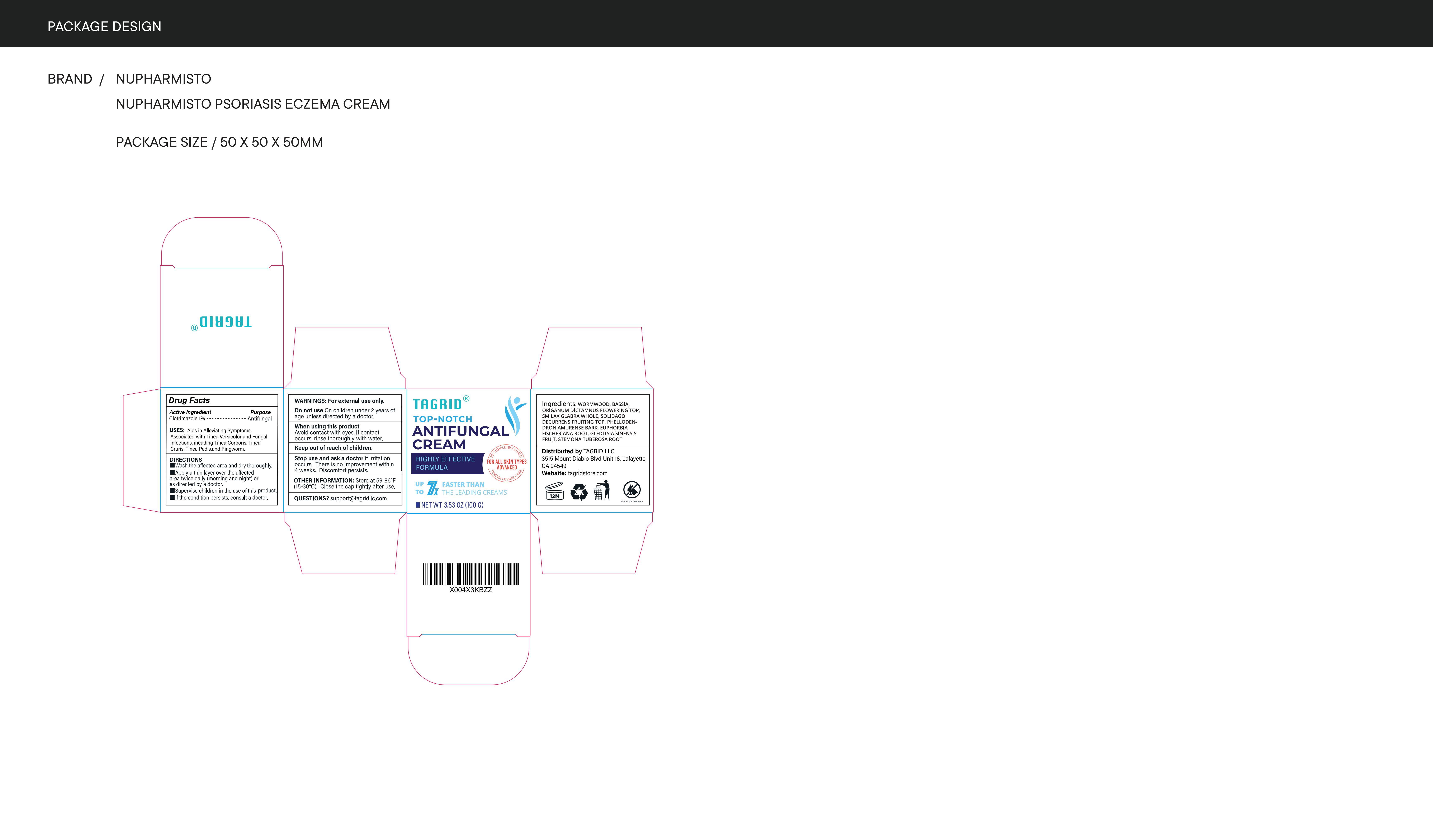 DRUG LABEL: Tagrid Antifungal Clotrimazole 1%
NDC: 85384-0019 | Form: CREAM
Manufacturer: TAGRID LLC
Category: otc | Type: HUMAN OTC DRUG LABEL
Date: 20230628

ACTIVE INGREDIENTS: CLOTRIMAZOLE 1 g/100 g
INACTIVE INGREDIENTS: WORMWOOD; BASSIA SCOPARIA FRUIT; ORIGANUM DICTAMNUS FLOWERING TOP; SMILAX GLABRA WHOLE; SOLIDAGO DECURRENS FRUITING TOP; PHELLODENDRON AMURENSE BARK; EUPHORBIA FISCHERIANA ROOT; GLEDITSIA SINENSIS FRUIT; STEMONA TUBEROSA ROOT

Active ingredient:

1. Clotrimazole 1%

PURPOSE

1. Antifungal

Uses:

1. Aids in Alleviating Symptoms.
2. Associated with Tinea Versicolor and Fungal infections, including Tinea Corporis, Tinea Cruris, Tinea Pedis, and Ringworm.

WARNINGS

For external use only.

Do not use:

- On children under 2 years of age unless directed by a doctor.

When using this product

- Avoid contact with eyes. If contact occurs, rinse thoroughly with water.

Stop use and ask a doctor if

- Irritation occurs.
- There is no improvement within 4 weeks.
- Discomfort persists.

Keep out of reach of children.

Directions

- Wash the affected area and dry thoroughly.
- Apply a thin layer over the affected area twice daily (morning and night) or as directed by a doctor.
- Supervise children in the use of this product.
- If the condition persists, consult a doctor.

Inactive Ingredients

- Wormwood
- Bassia
- Origanum Dictamnus Flowering Top
- Smilax Glabra Whole
- Solidago Decurrens Fruiting Top
- Phellodendron Amurense Bark
- Euphorbia Fischeriana Root
- Gleditsia Sinensis Fruit
- Stemona Tuberosa Root

Questions?

support@tagridstore.com